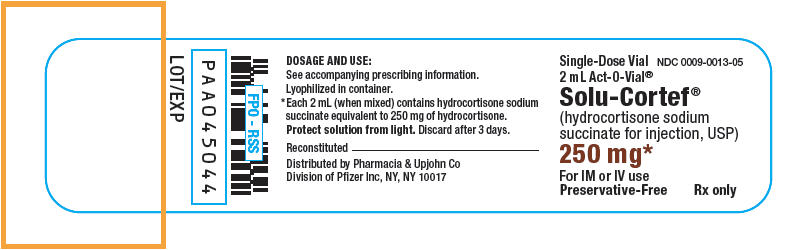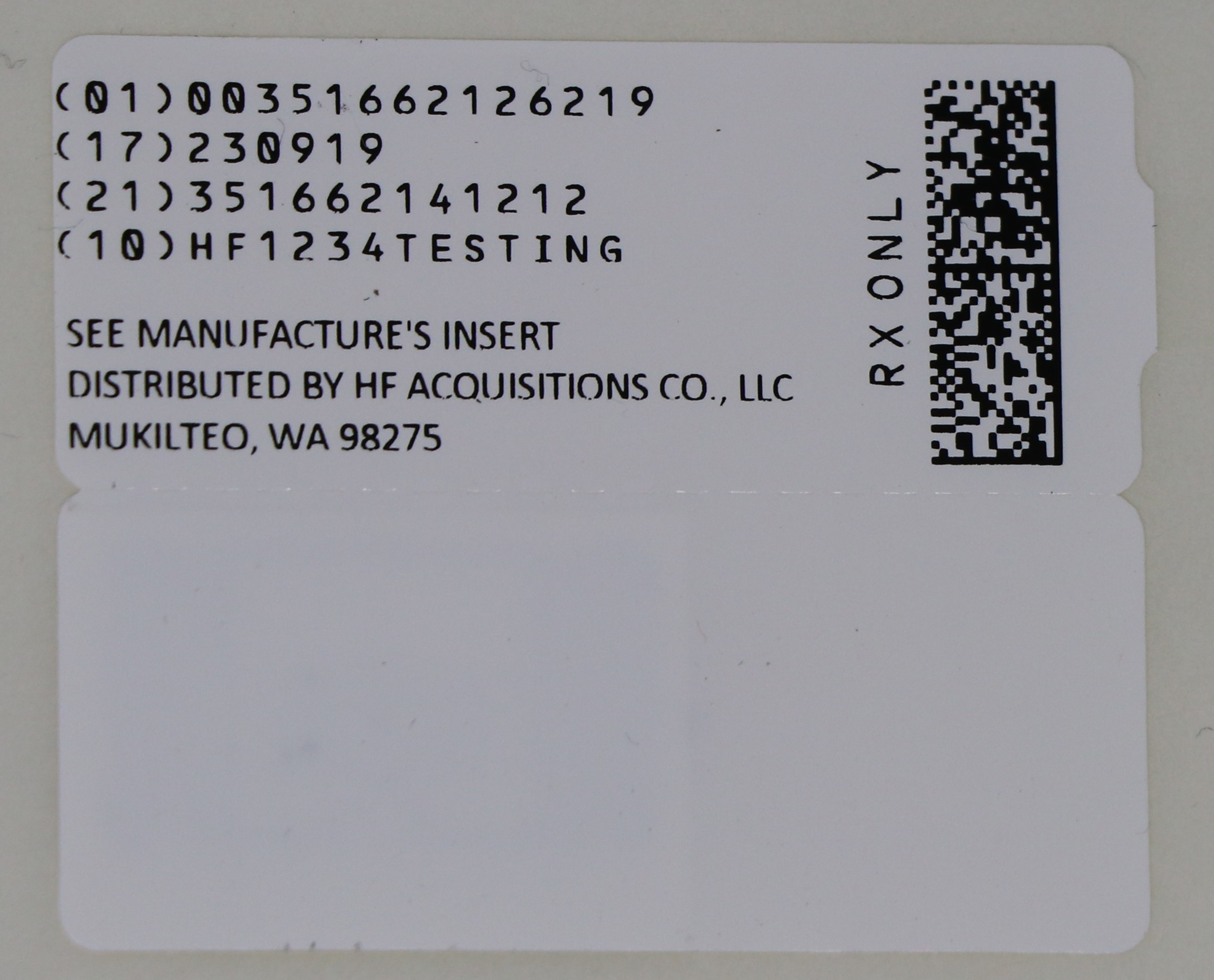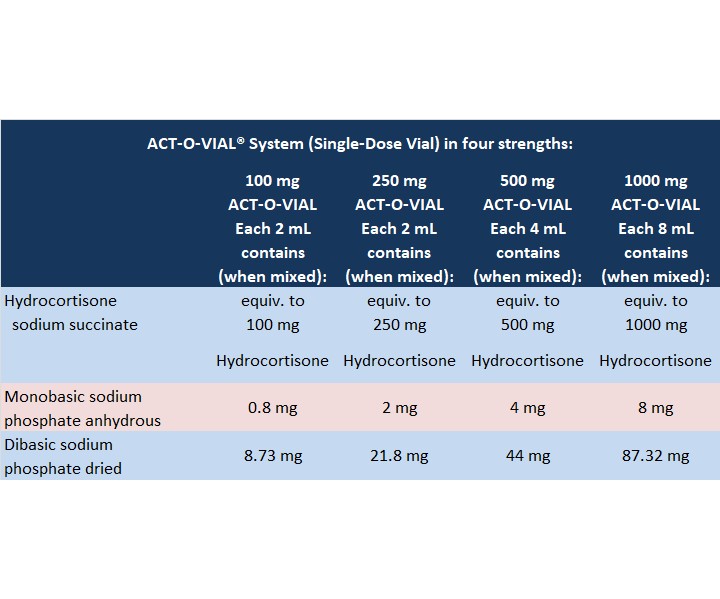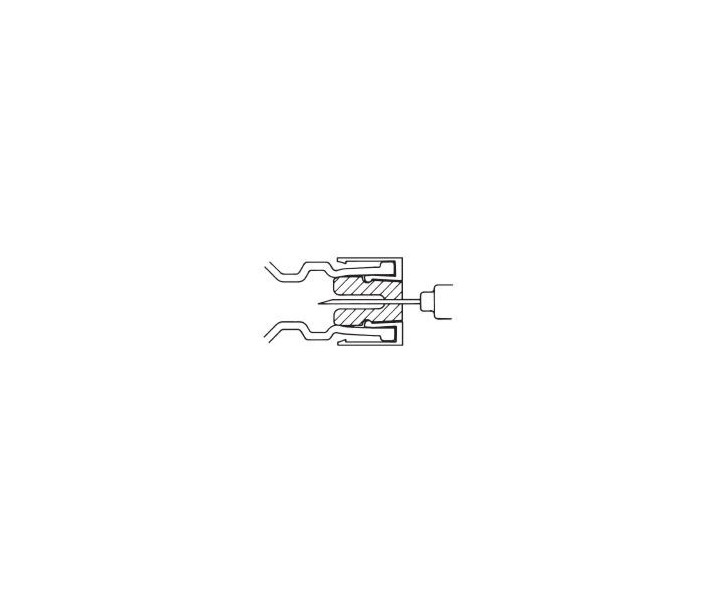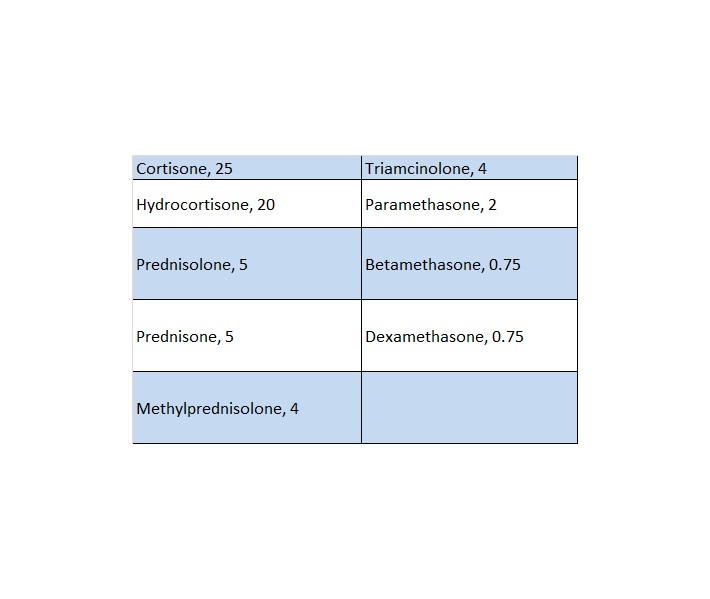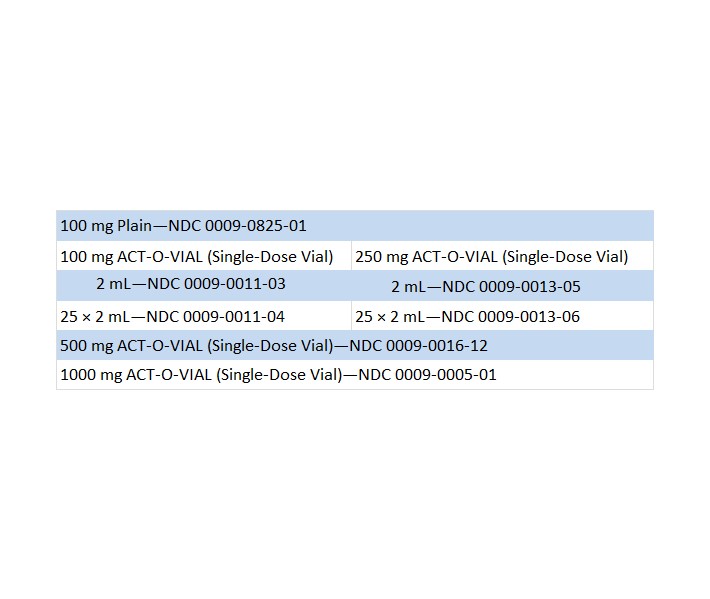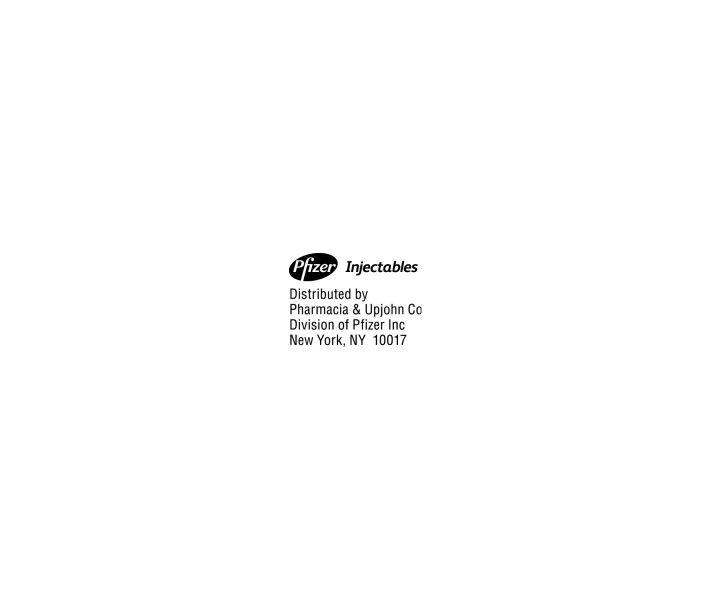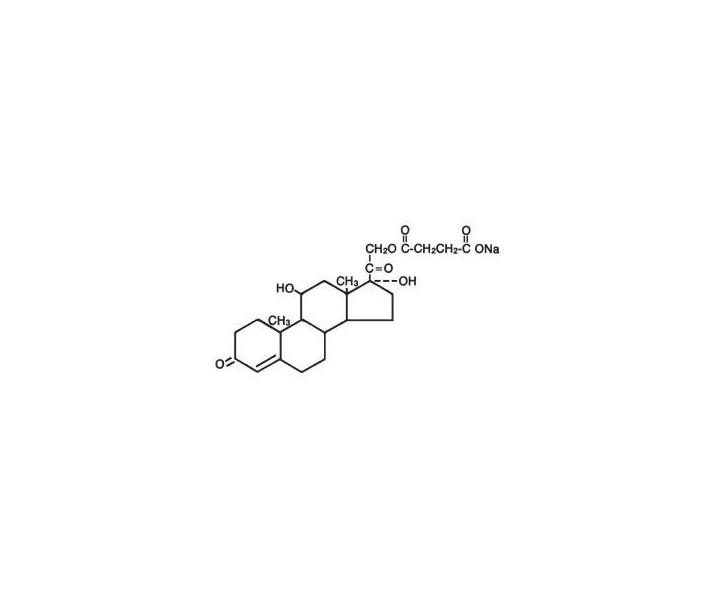 DRUG LABEL: SOLU-CORTEF
NDC: 51662-1262 | Form: INJECTION, POWDER, FOR SOLUTION
Manufacturer: HF Acquisition Co. LLC, DBA HealthFirst
Category: prescription | Type: HUMAN PRESCRIPTION DRUG LABEL
Date: 20240222

ACTIVE INGREDIENTS: HYDROCORTISONE SODIUM SUCCINATE 250 mg/2 mL
INACTIVE INGREDIENTS: SODIUM PHOSPHATE, MONOBASIC, ANHYDROUS 2 mg/2 mL; SODIUM PHOSPHATE, DIBASIC, UNSPECIFIED FORM 21.8 mg/2 mL

SOLU-CORTEF® 250mg 2mL ACT-O-VIAL®

SPL UNCLASSIFIED

For Intravenous or Intramuscular Administration

DESCRIPTION

SOLU-CORTEF Sterile Powder is an anti-inflammatory glucocorticoid that contains hydrocortisone sodium succinate as the active ingredient. SOLU-CORTEF Sterile Powder is available in several packages for intravenous or intramuscular administration.

100 mg Plain—Vials containing hydrocortisone sodium succinate equivalent to 100 mg hydrocortisone, 0.8 mg monobasic sodium phosphate anhydrous, 8.73 mg dibasic sodium phosphate dried. SOLU-CORTEF 100 mg plain does not contain diluent (see DOSAGE & ADMINISTRATION, Preparation of Solutions).

The diluent, as part of the packaging presentation for the ACT-O-VIAL® system, is comprised of Water for Injection only, and does not contain any preservative.

When necessary, the pH of each formula was adjusted with sodium hydroxide so that the pH of the reconstituted solution is within the USP specified range of 7 to 8.

The chemical name for hydrocortisone sodium succinate is pregn-4-ene-3,20-dione,21-(3-carboxy-1-oxopropoxy)-11,17-dihydroxy-, monosodium salt, (11β)- and its molecular weight is 484.52.

The structural formula is represented below:

Hydrocortisone sodium succinate is a white or nearly white, odorless, hygroscopic amorphous solid. It is very soluble in water and in alcohol, very slightly soluble in acetone, and insoluble in chloroform.

CLINICAL PHARMACOLOGY

Glucocorticoids, naturally occurring and synthetic, are adrenocortical steroids that are readily absorbed from the gastrointestinal tract.

Naturally occurring glucocorticoids (hydrocortisone and cortisone), which also have salt-retaining properties, are used as replacement therapy in adrenocortical deficiency states. Their synthetic analogs are primarily used for their anti-inflammatory effects in disorders of many organ systems.

Hydrocortisone sodium succinate has the same metabolic and anti-inflammatory actions as hydrocortisone. When given parenterally and in equimolar quantities, the two compounds are equivalent in biologic activity. The highly water-soluble sodium succinate ester of hydrocortisone permits the immediate intravenous administration of high doses of hydrocortisone in a small volume of diluent and is particularly useful where high blood levels of hydrocortisone are required rapidly. Following the intravenous injection of hydrocortisone sodium succinate, demonstrable effects are evident within one hour and persist for a variable period. Excretion of the administered dose is nearly complete within 12 hours. Thus, if constantly high blood levels are required, injections should be made every 4 to 6 hours. This preparation is also rapidly absorbed when administered intramuscularly and is excreted in a pattern similar to that observed after intravenous injection.

Glucocorticoids cause profound and varied metabolic effects. In addition, they modify the body's immune response to diverse stimuli.

INDICATIONS & USAGE

When oral therapy is not feasible, and the strength, dosage form, and route of administration of the drug reasonably lend the preparation to the treatment of the condition, the intravenous or intramusculat use of SOLU-CORTEF Sterile Powder is indicated as follows:

Allergic states

Control of severe or incapacitating allergic conditions intractable to adequate trials of conventional treatment in asthma, atopic dermatitis, contact dermatitis, drug hypersensitivity reactions, perennial or seasonal allergic rhinitis, serum sickness, transfusion reactions.

Dermatologic diseases

Bullous dermatitis herpetiformis, exfoliative erythroderma, mycosis fungoides, pemphigus, severe erythema multiforme (Stevens-Johnson syndrome).

Endocrine disorders

Primary or secondary adrenocortical insufficiency (hydrocortisone or cortisone is the drug of choice; synthetic analogs may be used in conjunction with mineralocorticoids where applicable; in infancy, mineralocorticoid supplementation is of particular importance), congenital adrenal hyperplasia, hypercalcemia associated with cancer, nonsuppurative thyroiditis.

Gastrointestinal diseases

To tide the patient over a critical period of the disease in regional enteritis (systemic therapy) and ulcerative colitis.

Hematologic disorders

Acquired (autoimmune) hemolytic anemia, congenital (erythroid) hypoplastic anemia (Diamond Blackfan anemia), idiopathic thrombocytopenic purpura in adults (intravenous administration only; intramuscular administration is contraindicated), pure red cell aplasia, select cases of secondary thrombocytopenia.

Miscellaneous

Trichinosis with neurologic or myocardial involvement, tuberculous meningitis with subarachnoid block or impending block when used concurrently with appropriate antituberculous chemotherapy.

Neoplastic diseases

For the palliative management of leukemias and lymphomas.

Nervous System

Acute exacerbations of multiple sclerosis; cerebral edema associated with primary or metastatic brain tumor, or craniotomy.

Ophthalmic diseases

Sympathetic ophthalmia, uveitis and ocular inflammatory conditions unresponsive to topical corticosteroids.

Renal diseases

To induce diuresis or remission of proteinuria in idiopathic nephrotic syndrome, or that due to lupus erythematosus.

Respiratory diseases

Berylliosis, fulminating or disseminated pulmonary tuberculosis when used concurrently with appropriate antituberculous chemotherapy, idiopathic eosinophilic pneumonias, symptomatic sarcoidosis.

Rheumatic disorders

As adjunctive therapy for short-term administration (to tide the patient over an acute episode or exacerbation) in acute gouty arthritis; acute rheumatic carditis; ankylosing spondylitis; psoriatic arthritis; rheumatoid arthritis, including juvenile rheumatoid arthritis (selected cases may require low-dose maintenance therapy). For the treatment of dermatomyositis, temporal arteritis, polymyositis, and systemic lupus erythematosus.

CONTRAINDICATIONS

SOLU-CORTEF Sterile Powder is contraindicated in systemic fungal infections and patients with known hypersensitivity to the product and its constituents.

Intramuscular corticosteroid preparations are contraindicated for idiopathic thrombocytopenic purpura.

SOLU-CORTEF Sterile Powder is contraindicated for intrathecal administration. Reports of severe medical events have been associated with this route of administration.

WARNINGS

Serious Neurologic Adverse Reactions with Epidural Administration

Serious neurologic events, some resulting in death, have been reported with epidural injection of corticosteroids. Specific events reported include, but are not limited to, spinal cord infarction, paraplegia, quadriplegia, cortical blindness, and stroke. These serious neurologic events have been reported with and without use of fluoroscopy. The safety and effectiveness of epidural administration of corticosteroids have not been established, and corticosteroids are not approved for this use.

General

Injection of SOLU-CORTEF may result in dermal and/or subdermal changes forming depressions in the skin at the injection site. In order to minimize the incidence of dermal and subdermal atrophy, care must be exercised not to exceed recommended doses in injections. Injection into the deltoid muscle should be avoided because of a high incidence of subcutaneous atrophy.

Rare instances of anaphylactoid reactions have occurred in patients receiving corticosteroid therapy (see ADVERSE REACTIONS).

Increased dosage of rapidly acting corticosteroids is indicated in patients on corticosteroid therapy subjected to any unusual stress before, during, and after the stressful situation.

Results from one multicenter, randomized, placebo-controlled study with methylprednisolone hemisuccinate, an IV corticosteroid, showed an increase in early (at 2 weeks) and late (at 6 months) mortality in patients with cranial trauma who were determined not to have other clear indications for corticosteroid treatment. High doses of systemic corticosteroids, including SOLU-CORTEF, should not be used for the treatment of traumatic brain injury.

Cardio-renal

Average and large doses of corticosteroids can cause elevation of blood pressure, salt and water retention, and increased excretion of potassium. These effects are less likely to occur with the synthetic derivatives except when used in large doses. Dietary salt restriction and potassium supplementation may be necessary. All corticosteroids increase calcium excretion.

Literature reports suggest an apparent association between use of corticosteroids and left ventricular free wall rupture after a recent myocardial infarction; therefore, therapy with corticosteroids should be used with great caution in these patients.

Endocrine

Hypothalamic-pituitary adrenal (HPA) axis suppression. Cushing's syndrome, and hyperglycemia. Monitor patients for these conditions with chronic use. Corticosteroids can produce reversible HPA axis suppression with the potential for glucocorticosteroid insufficiency after withdrawal of treatment. Drug induced secondary adrenocortical insufficiency may be minimized by gradual reduction of dosage. This type of relative insufficiency may persist for months after discontinuation of therapy; therefore, in any situation of stress occurring during that period, hormone therapy should be reinstituted.

Infections

General

Patients who are on corticosteroids are more susceptible to infections than are healthy individuals. There may be decreased resistance and inability to localize infection when corticosteroids are used. Infection with any pathogen (viral, bacterial, fungal, protozoan or helminthic) in any location of the body may be associated with the use of corticosteroids alone or in combination with other immunosuppressive agents.

These infections may be mild, but can be severe and at times fatal. With increasing doses of corticosteroids, the rate of occurrence of infectious complications increases. Corticosteroids may also mask some signs of current infection. Do not use intra-articularly, intrabursally or for intratendinous administration for local effect in the presence of acute local infection.

Fungal infections

Corticosteroids may exacerbate systemic fungal infections and therefore should not be used in the presence of such infections unless they are needed to control drug reactions. There have been cases reported in which concomitant use of amphotericin B and hydrocortisone was followed by cardiac enlargement and congestive heart failure (see CONTRAINDICATIONS and PRECAUTIONS: Drug Interactions, Amphotericin B injection and potassium-depleting agents).

Special pathogens

Latent disease may be activated or there may be an exacerbation of intercurrent infections due to pathogens, including those caused by Amoeba, Candida, Cryptococcus, Mycobacterium, Nocardia, Pneumocystis, and Toxoplasma.

It is recommended that latent amebiasis or active amebiasis be ruled out before initiating corticosteroid therapy in any patient who has spent time in the tropics or in any patient with unexplained diarrhea.

Similarly, corticosteroids should be used with great care in patients with known or suspected Strongyloides (threadworm) infestation. In such patients, corticosteroid-induced immunosuppression may lead to Strongyloides hyperinfection and dissemination with widespread larval migration, often accompanied by severe enterocolitis and potentially fatal gram-negative septicemia.

Corticosteroids should not be used in cerebral malaria. There is currently no evidence of benefit from steroids in this condition.

Tuberculosis

The use of corticosteroids in active tuberculosis should be restricted to those cases of fulminating or disseminated tuberculosis in which the corticosteroid is used for the management of the disease in conjunction with an appropriate antituberculous regimen.

If corticosteroids are indicated in patients with latent tuberculosis or tuberculin reactivity, close observation is necessary as reactivation of the disease may occur. During prolonged corticosteroid therapy, these patients should receive chemoprophylaxis.

Vaccination

Administration of live or live, attenuated vaccines is contraindicated in patients receiving immunosuppressive doses of corticosteroids. Killed or inactivated vaccines may be administered. However, the reponse to such vaccines cannot be predicted. Immunization procedures may be undertaken in patients who are receiving corticosteroids as replacement therapy (e.g., for Addison's disease).

Viral infections

Chicken pox and measles can have a more serious or even fatal course in pediatric and adult patients on corticosteroids. In pediatric and adult patients who have not had these diseases, particular care should be taken to avoid exposure. The contribution of the underlying disease and/or prior corticosteroid treatment to the risk is not known. If exposed to chicken pox, prophylaxis with varicella zoster immune globulin (VZIG) may be indicated. If exposed to measles, prophylaxis with immunoglobulin (IG) may be indicated. (See the respective package inserts for complete VZIG and IG prescribing information.) If chicken pox develops, treatment with antiviral agents should be considered.

Neurologic

Reports of severe medical events have been associated with the intrathecal route of administration (see ADVERSE REACTIONS, Neurologic/Psychiatric).

Ophthalmic

Use of corticosteroids may produce posterior subcapsular cataracts, glaucoma with possible damage to the optic nerves, and may enhance the establishment of secondary ocular infections due to bacteria, fungi, or viruses. The use of oral corticosteroids is not recommended in the treatment of optic neuritis and may lead to an increase in the risk of new episodes. Corticosteroids should be used cautiously in patients with ocular herpes simplex because of corneal perforation. Corticosteroids should not be used in active ocular herpes simplex.

PRECAUTIONS

General

This product, like many other steroid formulations, is sensitive to heat. Therefore, it should not be autoclaved when it is desirable to sterilize the exterior of the vial. The lowest possible dose of corticosteroid should be used to control the condition under treatment. When reduction in dosage is possible, the reduction should be gradual.

Since complications of treatment with glucocorticoids are dependent on the size of the dose and the duration of treatment, a risk/benefit decision must be made in each individual case as to dose and duration of treatment and as to whether daily or intermittent therapy should be used.

Kaposi's sarcoma has been reported to occur in patients receiving corticosteroid therapy, most often for chronic conditions. Discontinuation of corticosteroids may result in clinical improvement.

Cardio-renal

As sodium retention with resultant edema and potassium loss may occur in patients receiving corticosteroids, these agents should be used with caution in patients with congestive heart failure, hypertension, or renal insufficiency.

Endocrine

Drug-induced secondary adrenocortical insufficiency may be minimized by gradual reduction of dosage. This type of relative insufficiency may persist for months after discontinuation of therapy; therefore, in any situation of stress occurring during that period, hormone therapy should be reinstituted. Metabolic clearance of corticosteroids is decreased in hypothyroid patients and increased in hyperthyroid patients. Changes in thyroid status of the patient may necessitate adjustment in dosage.

Gastrointestinal

Steroids should be used with caution in active or latent peptic ulcers, diverticulitis, fresh intestinal anastomoses, and non-specific ulcerative colitis, since they may increase the risk of a perforation. Signs of peritoneal irritation following gastrointestinal perforation in patients receiving corticosteroids may be minimal or absent.

There is an enhanced effect due to decreased metabolism of corticosteroids in patients with cirrhosis.

Musculoskeletal

Corticosteroids decrease bone formation and increase bone resorption both through their effect on calcium regulation (e.g., decreasing absorption and increasing excretion) and inhibition of osteoblast function. This, together with a decrease in the protein matrix of the bone secondary to an increase in protein catabolism, and reduced sex hormone production, may lead to inhibition of bone growth in pediatric patients and the development of osteoporosis at any age. Special consideration should be given to patients at increased risk of osteoporosis (i.e., postmenopausal women) before initiating corticosteroid therapy.

Local injection of a steroid into a previously infected site is not usually recommended.

Neurologic-psychiatric

Although controlled clinical trials have shown corticosteroids to be effective in speeding the resolution of acute exacerbations of multiple sclerosis, they do not show that corticosteroids affect the ultimate outcome or natural history of the disease. The studies do show that relatively high doses of corticosteroids are necessary to demonstrate a significant effect. (See DOSAGE & ADMINISTRATION.)

An acute myopathy has been observed with the use of high doses of corticosteroids, most often occurring in patients with disorders of neuromuscular transmission (e.g., myasthenia gravis), or in patients receiving concomitant therapy with neuromuscular blocking drugs (e.g., pancuronium). This acute myopathy is generalized, may involve ocular and respiratory muscles, and may result in quadriparesis. Elevation of creatine kinase may occur. Clinical improvement or recovery after stopping corticosteroids may require weeks to years.

Psychic derangements may appear when corticosteroids are used, ranging from euphoria, insomnia, mood swings, personality changes, and severe depression to frank psychotic manifestations. Also, existing emotional instability or psychotic tendencies may be aggravated by corticosteroids.

Ophthalmic

Intraocular pressure may become elevated in some individuals. If steroid therapy is continued for more than 6 weeks, intraocular pressure should be monitored.

Other

Pheochromocytoma crisis, which can be fatal, has been reported after administration of systemic corticosteroids. In patients with suspected pheochromocytoma, consider the risk of pheochromocytoma crisis prior to administering corticosteroids.

Information for Patients

Patients should be warned not to discontinue the use of corticosteroids abruptly or without medical supervision, to advise any medical attendants that they are taking corticosteroids, and to seek medical advice at once should they develop fever or other signs of infection.

Persons who are on corticosteroids should be warned to avoid exposure to chicken pox or measles. Patients should also be advised that if they are exposed, medical advice should be sought without delay.

Drug Interactions

Aminoglutethimide

Aminoglutethimide may lead to a loss of corticosteroid-induced adrenal suppression.

Amphotericin B injection and potassium-depleting agents

When corticosteroids are administered concomitantly with potassium-depleting agents (e.g., amphotericin B, diuretics), patients should be observed closely for development of hypokalemia. There have been cases reported in which concomitant use of amphotericin B and hydrocortisone was followed by cardiac enlargement and congestive heart failure.

Antibiotics

Macrolide antibiotics have been reported to cause a significant decrease in corticosteroid clearance (see PRECAUTIONS: Drug Interactions, Hepatic Enzyme Inhibitors).

Anticholinesterases

Concomitant use of anticholinesterase agents and corticosteroids may produce severe weakness in patients with myasthenia gravis. If possible, anticholinesterase agents should be withdrawn at least 24 hours before initiating corticosteroid therapy.

Anticoagulants, oral

Coadministration of corticosteroids and warfarin usually results in inhibition of response to warfarin, although there have been some conflicting reports. Therefore, coagulation indices should be monitored frequently to maintain the desired anticoagulant effect.

Antidiabetics

Because corticosteroids may increase blood glucose concentrations, dosage adjustments of antidiabetic agents may be required.

Antitubercular drugs

Serum concentrations of isoniazid may be decreased.

Cholestyramine

Cholestyramine may increase the clearance of corticosteroids.

Cyclosporine

Increased activity of both cyclosporine and corticosteroids may occur when the two are used concurrently. Convulsions have been reported with this concurrent use.

Digitalis glycosides

Patients on digitalis glycosides may be at increased risk of arrhythmias due to hypokalemia.

Estrogens, including oral contraceptives

Estrogens may decrease the hepatic metabolism of certain corticosteroids, thereby increasing their effect.

Hepatic Enzyme Inducers (e.g., barbiturates, phenytoin, carbamazepine, rifampin)

Drugs that induce cytochrome P450 3A4 enzyme activity may enhance the metabolism of corticosteroids and require that the dosage of the corticosteroid be increased.

Hepatic Enzyme Inhibitors (e.g., ketoconazole, macrolide antibiotics such as erythromycin and troleandomycin)

Drugs that inhibit cytochrome P450 3A4 have the potential to result in increased plasma concentrations of corticosteroids.

Ketoconazole

Ketoconazole has been reported to significantly decrease the metabolism of certain corticosteroids by up to 60%, leading to an increased risk of corticosteroid side effects.

Nonsteroidal anti-inflammatory drugs (NSAIDs)

Concomitant use of aspirin (or other nonsteroidal anti-inflammatory agents) and corticosteroids increases the risk of gastrointestinal side effects. Aspirin should be used cautiously in conjunction with corticosteroids in hypoprothrombinemia. The clearance of salicylates may be increased with concurrent use of corticosteroids.

Skin tests

Corticosteroids may suppress reactions to skin tests.

Vaccines

Patients on prolonged corticosteroid therapy may exhibit a diminished response to toxoids and live or inactivated vaccines due to inhibition of antibody response. Corticosteroids may also potentiate the replication of some organisms contained in live attenuated vaccines. Routine administration of vaccines or toxoids should be deferred until corticosteroid therapy is discontinued if possible (see WARNINGS: Infections, Vaccination).

Carcinogenesis, Mutagenesis, Impairment of Fertility

No adequate studies have been conducted in animals to determine whether corticosteroids have a potential for carcinogenesis or mutagenesis.

Steroids may increase or decrease motility and number of spermatozoa in some patients.

Corticosteroids have been shown to impair fertility in male rats.

Pregnancy

Teratogenic Effects

Corticosteroids have been shown to be teratogenic in many species when given in doses equivalent to the human dose. Animal studies in which corticosteroids have been given to pregnant mice, rats, and rabbits have yielded an increased incidence of cleft palate in the offspring. There are no adequate and well-controlled studies in pregnant women. Corticosteroids should be used during pregnancy only if the potential benefit justifies the potential risk to the fetus. Infants born to mothers who have received corticosteroids during pregnancy should be carefully observed for signs of hypoadrenalism.

Nursing Mothers

Systemically administered corticosteroids appear in human milk and could suppress growth, interfere with endogenous corticosteroid production, or cause other untoward effects. Because of the potential for serious adverse reactions in nursing infants from corticosteroids, a decision should be made whether to continue nursing or discontinue the drug, taking into account the importance of the drug to the mother.

Pediatric Use

The efficacy and safety of corticosteroids in the pediatric population are based on the well-established course of effect of corticosteroids, which is similar in pediatric and adult populations. Published studies provide evidence of efficacy and safety in pediatric patients for the treatment of nephrotic syndrome (>2 years of age) and aggressive lymphomas and leukemias (>1 month of age). Other indications for pediatric use of corticosteroids (e.g., severe asthma and wheezing) are based on adequate and well-controlled trials conducted in adults, on the premises that the course of the diseases and their pathophysiology are considered to be substantially similar in both populations.

The adverse effects of corticosteroids in pediatric patients are similar to those in adults (see ADVERSE REACTIONS). Like adults, pediatric patients should be carefully observed with frequent measurements of blood pressure, weight, height, intraocular pressure, and clinical evaluation for the presence of infection, psychosocial disturbances, thromboembolism, peptic ulcers, cataracts, and osteoporosis. Pediatric patients who are treated with corticosteroids by any route, including systemically administered corticosteroids, may experience a decrease in their growth velocity. This negative impact of corticosteroids on growth has been observed at low systemic doses and in the absence of laboratory evidence of HPA axis suppression (i.e., cosyntropin stimulation and basal cortisol plasma levels). Growth velocity may therefore be a more sensitive indicator of systemic corticosteroid exposure in pediatric patients than some commonly used tests of HPA axis function. The linear growth of pediatric patients treated with corticosteroids should be monitored, and the potential growth effects of prolonged treatment should be weighed against clinical benefits obtained and the availability of treatment alternatives. In order to minimize the potential growth effects of corticosteroids, pediatric patients should be titrated to the lowest effective dose.

Geriatric Use

Clinical studies did not include sufficient numbers of subjects aged 65 and over to determine whether they respond differently from younger subjects. Other reported clinical experience has not identified differences in responses between the elderly and younger patients. In general, dose selection for an elderly patient should be cautious, usually starting at the low end of the dosing range, reflecting the greater frequency of decreased hepatic, renal, or cardiac function, and of concomitant disease or other drug therapy.

ADVERSE REACTIONS

The following adverse reactions have been reported with SOLU-CORTEF or other corticosteroids:

Allergic reactions: Allergic or hypersensitivity reactions, anaphylactoid reaction, anaphylaxis, angioedema.

Blood and lymphatic system disorders: Leukocytosis.

Cardiovascular: Bradycardia, cardiac arrest, cardiac arrhythmias, cardiac enlargement, circulatory collapse, congestive heart failure, fat embolism, hypertension, hypertrophic cardiomyopathy in premature infants, myocardial rupture following recent myocardial infarction (see WARNINGS), pulmonary edema, syncope, tachycardia, thromboembolism, thrombophlebitis, vasculitis.

Dermatologic: Acne, allergic dermatitis, burning or tingling (especially in the perineal area, after intravenous injection), cutaneous and subcutaneous atrophy, dry scaly skin, ecchymoses and petechiae, edema, erythema, hyperpigmentation, hypopigmentation, impaired wound healing, increased sweating, rash, sterile abscess, striae, suppressed reactions to skin tests, thin fragile skin, thinning scalp hair, urticaria.

Endocrine: Decreased carbohydrate and glucose tolerance, development of cushingoid state, glycosuria, hirsutism, hypertrichosis, increased requirements for insulin or oral hypoglycemic agents in diabetes, manifestations of latent diabetes mellitus, menstrual irregularities, secondary adrenocortical and pituitary unresponsiveness (particularly in times of stress, as in trauma, surgery, or illness), suppression of growth in pediatric patients.

Fluid and electrolyte disturbances: Congestive heart failure in susceptible patients, fluid retention, hypokalemic alkalosis, potassium loss, sodium retention.

Gastrointestinal: Abdominal distention, bowel/bladder dysfunction (after intrathecal administration), elevation in serum liver enzyme levels (usually reversible upon discontinuation), hepatomegaly, increased appetite, nausea, pancreatitis, peptic ulcer with possible perforation and hemorrhage, perforation of the small and large intestine (particularly in patients with inflammatory bowel disease), ulcerative esophagitis.

Metabolic: Negative nitrogen balance due to protein catabolism.

Musculoskeletal: Aseptic necrosis of femoral and humeral heads, Charcot-like arthropathy, loss of muscle mass, muscle weakness, osteoporosis, pathologic fracture of long bones, postinjection flare (following intra-articular use), steroid myopathy, tendon rupture, vertebral compression fractures.

Neurologic/Psychiatric: Convulsions, depression, emotional instability, euphoria, headache, increased intracranial pressure with papilledema (pseudotumor cerebri) usually following discontinuation of treatment, insomnia, mood swings, neuritis, neuropathy, paresthesia, personality changes, psychic disorders, vertigo. Arachnoiditis, meningitis, paraparesis/paraplegia, and sensory disturbances have occurred after intrathecal administration (see WARNINGS: Neurologic), epidural lipomatosis.

Ophthalmic: Central serous chorioretinopathy, exophthalmoses, glaucoma, increased intraocular pressure, posterior subcapsular cataracts, rare instances of blindness associated with periocular injections.

Other: Abnormal fat deposits, decreased resistance to infection, hiccups, increased or decreased motility and number of spermatozoa, injection site infections following non-sterile administration (see WARNINGS), malaise, moon face, weight gain.

OVERDOSAGE

Treatment of acute overdosage is by supportive and symptomatic therapy. For chronic overdosage in the face of severe disease requiring continuous steroid therapy, the dosage of the corticosteroid may be reduced only temporarily, or alternate day treatment may be introduced.

DOSAGE & ADMINISTRATION

Because of possible physical incompatilitbilites, SOLU-CORTEF should not be diluted or mixed with other solutions.

Parenteral drug products should be inspected visually for particulate matter and discoloration prior to administration, whenever solution and container permit.

This preparation may be administered by intravenous injection, by intravenous infusion, or by intramuscular injection, the preferred method for initial emergency use being intravenous injection. Following the initial emergency period, consideration should be given to employing a longer acting injectable preparation or an oral preparation.

Therapy is initiated by administering SOLU-CORTEF Sterile Powder intravenously over a period of 30 seconds (e.g., 100 mg) to 10 minutes (e.g., 500 mg or more). In general, high dose corticosteroid therapy should be continued only until the patient's condition has stabilized, usually not beyond 48 to 72 hours. When high dose hydrocortisone therapy must be continued beyond 48–72 hours, hypernatremia may occur. Under such circumstances, it may be desirable to replace SOLU-CORTEF with a corticoid such as methylprednisolone sodium succinate which causes little or no sodium retention.

The initial dose of SOLU-CORTEF Sterile Powder is 100 mg to 500 mg, depending on the specific disease entity being treated. However, in certain overwhelming, acute, life-threatening situations, administration in dosages exceeding the usual dosages may be justified and may be in multiples of the oral dosages.

This dose may be repeated at intervals of 2, 4, or 6 hours as indicated by the patient's response and clinical condition.

It Should Be Emphasized that Dosage Requirements Are Variable and Must Be Individualized on the Basis of the Disease Under Treatment and the Response of the Patient. After a favorable response is noted, the proper maintenance dosage should be determined by decreasing the initial drug dosage in small decrements at appropriate time intervals until the lowest dosage that maintains an adequate clinical response is reached. Situations that may make dosage adjustments necessary are changes in clinical status secondary to remissions or exacerbations in the disease process, the patient's individual drug responsiveness, and the effect of patient exposure to stressful situations not directly related to the disease entity under treatment. In this latter situation, it may be necessary to increase the dosage of the corticosteroid for a period of time consistent with the patient's condition. If after long-term therapy the drug is to be stopped, it is recommended that it be withdrawn gradually rather than abruptly.

In the treatment of acute exacerbations of multiple sclerosis, daily doses of 800 mg of hydrocortisone for a week followed by 320 mg every other day for one month are recommended (see PRECAUTIONS, Neurologic-psychiatric).

In pediatric patients, the initial dose of hydrocortisone may vary depending on the specific disease entity being treated. The range of initial doses is 0.56 to 8 mg/kg/day in three or four divided doses (20 to 240 mg/m2bsa/day). For the purpose of comparison, the following is the equivalent milligram dosage of the various glucocorticoids:

These dose relationships apply only to oral or intravenous administration of these compounds. When these substances or their derivatives are injected intramuscularly or into joint spaces, their relative properties may be greatly altered.

Preparation of Solutions 100 mg Plain

For intravenous or intramuscular injection, prepare solution by aseptically adding not more than 2 mL of Bacteriostatic Water for Injection or Bacteriostatic Sodium Chloride Injection to the contents of one vial. For intravenous infusion, first prepare solution by adding not more than 2 mL of Bacteriostatic Water for Injection to the vial; this solution may then be added to 100 to 1000 mL of the following: 5% dextrose in water (or isotonic saline solution or 5% dextrose in isotonic saline solution if patient is not on sodium restriction).

DIRECTIONS FOR USING THE ACT-O-VIAL SYSTEM

Press down on plastic activator to force diluent into the lower compartment.
Gently agitate to effect solution.
Remove plastic tab covering center of stopper.
Sterilize top of stopper with a suitable germicide.
Insert needle squarely through center of stopper until tip is just visible. Invert vial and withdraw dose.

Further dilution is not necessary for intravenous or intramuscular injection. For intravenous infusion, first prepare solution as just described. The 100 mg solution may then be added to 100 to 1000 mL of 5% dextrose in water (or isotonic saline solution or 5% dextrose in isotonic saline solution if patient is not on sodium restriction). The 250 mg solution may be added to 250 to 1000 mL, the 500 mg solution may be added to 500 to 1000 mL, and the 1000 mg solution to 1000 mL of the same diluents. In cases where administration of a small volume of fluid is desirable, 100 mg to 3000 mg of SOLU-CORTEF may be added to 50 mL of the above diluents. The resulting solutions are stable for at least 4 hours and may be administered either directly or by IV piggyback.

When reconstituted as directed, pH's of the solutions range from 7 to 8 and the tonicities are: 100 mg ACT-O-VIAL, 0.36 osmolar; 250 mg ACT-O-VIAL, 500 mg ACT-O-VIAL, and 1000 mg ACT-O-VIAL, 0.57 osmolar. (Isotonic saline=0.28 osmolar.)

HOW SUPPLIED

SOLU-CORTEF® is supplied in the following dosage forms.
NDC 51662-1262-1
SOLU-CORTEF® 250mg 2mL ACT-O-VIAL®

HF Acquisition Co LLC, DBA HealthFirst
Mukilteo, WA 98275

Also supplied in the following manufacture supplied dosage forms

SOLU-CORTEF Sterile Powder is available in the following packages:

STORAGE CONDITIONS

Store unreconstituted product at controlled room temperature 20° to 25°C (68° to 77°F).

Store solution at controlled room temperature 20° to 25°C (68° to 77°F) and protect from light. Use solution only if it is clear. Unused solution should be discarded after 3 days.

This product's label may have been updated. For current full prescribing information please visit www.pfizer.com

SPL UNCLASSIFIED

LAB-0424-9.0
October 2016

PRINCIPLE DISPLAY PANEL, VIAL

Single-Dose Vial
2 mL Act-O-Vial®
NDC 0009-0013-05

Solu-Cortef®

(hydrocortisone sodium
succinate for injection, USP)

250 mg*

For IM or IV use
Preservative-Free
Rx only